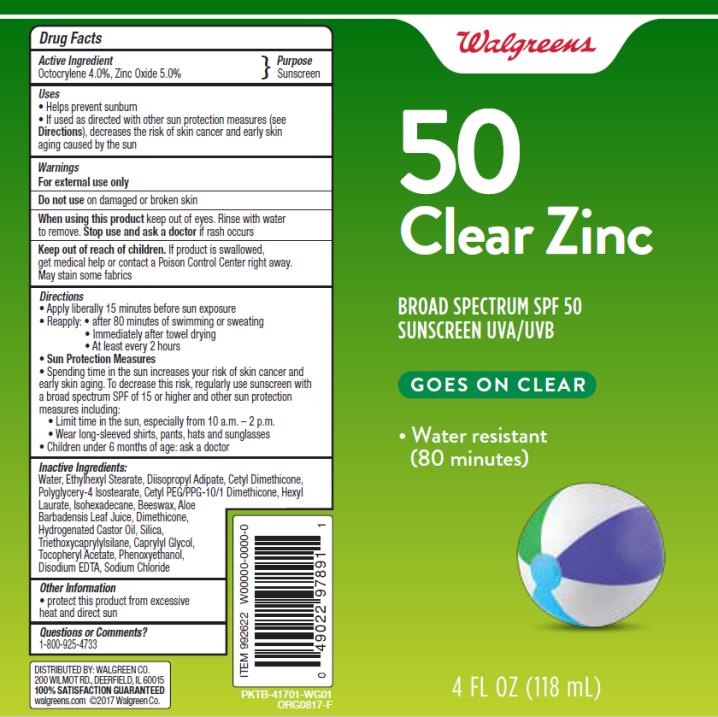 DRUG LABEL: Walgreens sunscreen Clear Zinc SPF50
NDC: 0363-9922 | Form: LOTION
Manufacturer: Walgreen Company
Category: otc | Type: HUMAN OTC DRUG LABEL
Date: 20171005

ACTIVE INGREDIENTS: OCTOCRYLENE 4 g/100 g; ZINC OXIDE 5 g/100 g
INACTIVE INGREDIENTS: WATER; ETHYLHEXYL STEARATE; DIISOPROPYL ADIPATE; CETYL PEG/PPG-10/1 DIMETHICONE (HLB 3); POLYGLYCERYL-4 ISOSTEARATE; CETYL DIMETHICONE 25; HEXYL LAURATE; ISOHEXADECANE; YELLOW WAX; ALOE VERA LEAF; DIMETHICONE; HYDROGENATED CASTOR OIL; SILICON DIOXIDE; TRIETHOXYCAPRYLYLSILANE; CAPRYLYL GLYCOL; ALPHA-TOCOPHEROL ACETATE; PHENOXYETHANOL; EDETATE DISODIUM ANHYDROUS; SODIUM CHLORIDE

WAG Sun Clear zinc spf50 4z

Walgreens sunscreen Clear Zinc SPF50

Walgreens sunscreen Clear Zinc SPF50

Active Ingredients

Octocrylene 4%, Zinc Oxide 5%

Purpose

Sunscreen

Uses

- helps prevent sunburn

• if used as directed with other sun protection measures (see Directions), decreases the risk of skin cancer and early skin aging caused by the sun

Warnings

For external use only

Do not use

on damaged or broken skin

When using this product

keep out of eyes. Rinse with water to remove.

Stop use and ask a doctor

if rash occurs

Keep out of reach of children.

If swallowed, get medical help or contact a Poison Control Center right away.

Directions

- apply liberally 15 minutes before sun exposure
- Sun Protection Measures. Spending time in the sun increases your risk of skin cancer and early skin aging. To decrease this risk, regularly use a sunscreen with a Broad Spectrum SPF of 15 or higher and other sun protection measures including:
- children under 6 months: Ask a doctor

• reapply:

• after 80 minutes of swimming or sweating

• immediately after towel drying

• at least every 2 hours

• limit time in the sun, especially from 10 a.m. - 2 p.m.

• wear long-sleeve shirts, pants, hats, and sunglasses

Inactive Ingredients

Deionized Water, Ethylhexyl Stearate, Disopropyl Adipate, Cetyl Dimethicone, Polyglycery-4 Isosteate, Cetyl PEG/PPG-10/1 Dimethicone, Hexyl Laurate, Isohexadecane, Beeswax, Aloe Barbadensis Leaf Juice, Dimethicone, Hydrogenated Castor Oil, Silica, Triethoxycaprylylsilane, Caprylyl Glycol, Tocopherol Acetate, Phenoxyethanol, Disodium EDTA, Sodium Chloride

Other Information

• for use on skin only. Avoid contact with fabric

• protect this product from excessive heat and direct sun

Questions or comments?

www.walgreens.com or call toll free 1-800-XXX-XXXX

PRINCIPAL DISPLAY PANEL

50
Clear Zinc
Broad Spectrum SPF 50
Sunscreen UVA/ UVB
4 FL OZ (118 mL)